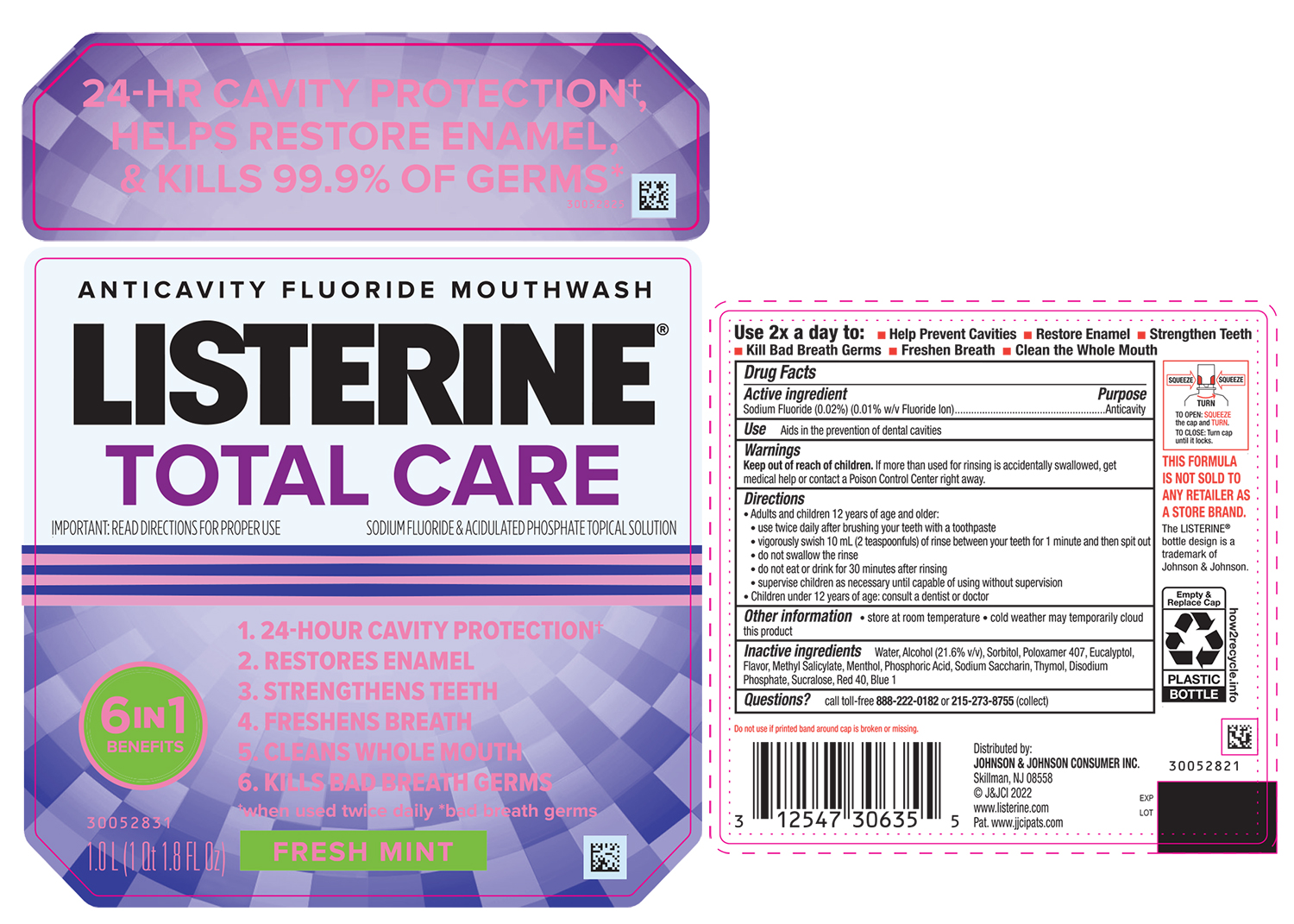 DRUG LABEL: Listerine Total Care Fresh Mint Anticavity Fluoride
NDC: 69968-0787 | Form: MOUTHWASH
Manufacturer: Kenvue Brands LLC
Category: otc | Type: HUMAN OTC DRUG LABEL
Date: 20250228

ACTIVE INGREDIENTS: SODIUM FLUORIDE 0.1 mg/1 mL
INACTIVE INGREDIENTS: WATER; SORBITOL; ALCOHOL; POLOXAMER 407; EUCALYPTOL; METHYL SALICYLATE; THYMOL; PHOSPHORIC ACID; MENTHOL, UNSPECIFIED FORM; SODIUM PHOSPHATE, DIBASIC, ANHYDROUS; SACCHARIN SODIUM; SUCRALOSE; FD&C RED NO. 40; FD&C BLUE NO. 1

Listerine Total Care Fresh Mint Anticavity Fluoride Mouthwash

Drug Facts

Active ingredient

Sodium Fluoride 0.02% (0.01% w/v Fluoride ion)

Purpose

Anticavity

Use

Aids in the prevention of dental cavities

Warnings

Keep out of reach of children. If more than used for rinsing is accidentally swallowed, get medical help or contact a Poison Control Center right away.

Directions

- Adults and children 12 years of age and older:
  - use twice daily after brushing your teeth with a toothpaste
  - vigorously swish 10 mL (2 teaspoonfuls) of rinse between your teeth for 1 minute and then spit out
  - do not swallow the rinse
  - do not eat or drink for 30 minutes after rinsing
  - supervise children as necessary until capable using without supervision
- Children under 12 years of age: consult a dentist or doctor

Other information

- store at room temperature
- cold weather may temporarily cloud this product

Inactive Ingredients

Water, Alcohol (21.6% v/v),Sorbitol, Poloxamer 407,Eucalyptol,Flavor,Methyl Salicylate,Menthol,Phosphoric Acid,Sodium Saccharin

Thymol,Disodium Phosphate, Sucralose, Red 40, Blue 1

Questions?

call toll-free 888-222-0182 or 215-273-8755 (collect)

Distributed by:
JOHNSON & JOHNSON CONSUMER INC.
Skillman, NJ 08558

PRINCIPAL DISPLAY PANEL - 1000 mL Bottle Label

ANTICAVITY FLUORIDE MOUTHWASH

LISTERINE®

TOTAL CARE

IMPORTANT: READ DIRECTIONS FOR PROPER USE.

SODIUM FLUORIDE & ACIDULATED PHOSPHATE TOPICAL SOLUTION

6 IN 1

BENEFITS

1. 24- HOUR CAVITY PROTECTION+

2. RESTORES ENAMEL

3. STRENGTHENS TEETH

4. FRESHENS BREATH

5. CLEANS THE WHOLE MOUTH

6. KILLS BAD BREATH GERMS

+When used twice daily * bad breath germs

FRESH MINT

1.0 L (1 Qt 1.8 fl oz)